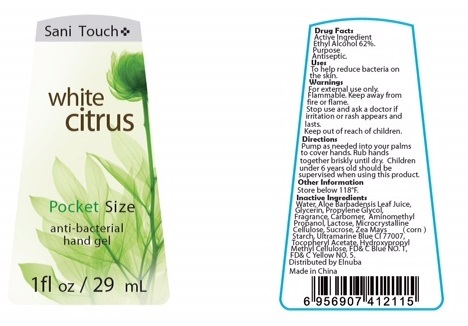 DRUG LABEL: anti-bacterial hand gel
NDC: 69909-001 | Form: GEL
Manufacturer: GASSER, MOHAMED
Category: otc | Type: HUMAN OTC DRUG LABEL
Date: 20150611

ACTIVE INGREDIENTS: ALCOHOL 62 mL/100 mL
INACTIVE INGREDIENTS: CELLULOSE, MICROCRYSTALLINE; WATER; ALOE VERA LEAF; GLYCERIN; PROPYLENE GLYCOL; CARBOMER INTERPOLYMER TYPE A (55000 CPS); SUCROSE; STARCH, CORN; ULTRAMARINE BLUE; .ALPHA.-TOCOPHEROL ACETATE; HYPROMELLOSES; FD&C BLUE NO. 1; AMINOMETHYLPROPANOL; LACTOSE; FD&C YELLOW NO. 5

Active Ingredient:
Ethyl Alcohol 62%.

Purpose:

Antiseptic

Warnings:

For external use only.

Flammable. Keep away from fire or flame.

Stop use and ask a doctor if irritation or rash appears and lasts.

Keep out of reach of children.

Directions:
Pump as needed into your palms to cover hands. Rub hands together briskly until dry. Children under 6 years old should be supervised when using this product.

INACTIVE INGREDIENT

Inactive ingredients: Water, Aloe Barbadenis Leaf Juice, Glycerin, Propylene Glycol, Fragrance, Carbomer, Aminomethyl Propanol, Lactose, Microcrystalline Cellulose, Sucrose, Zea Mays (corn) Starch, Ultramarine Blue CI 77007, Tocopheryl Acetate, Hydroxypropyl Methyl Cellulose, FD&C Blue NO.1, FD&C Yellow NO.5.

Other information: Store below 118 F.

INDICATIONS AND USAGE

Uses: To help reduce bacteria on the skin.